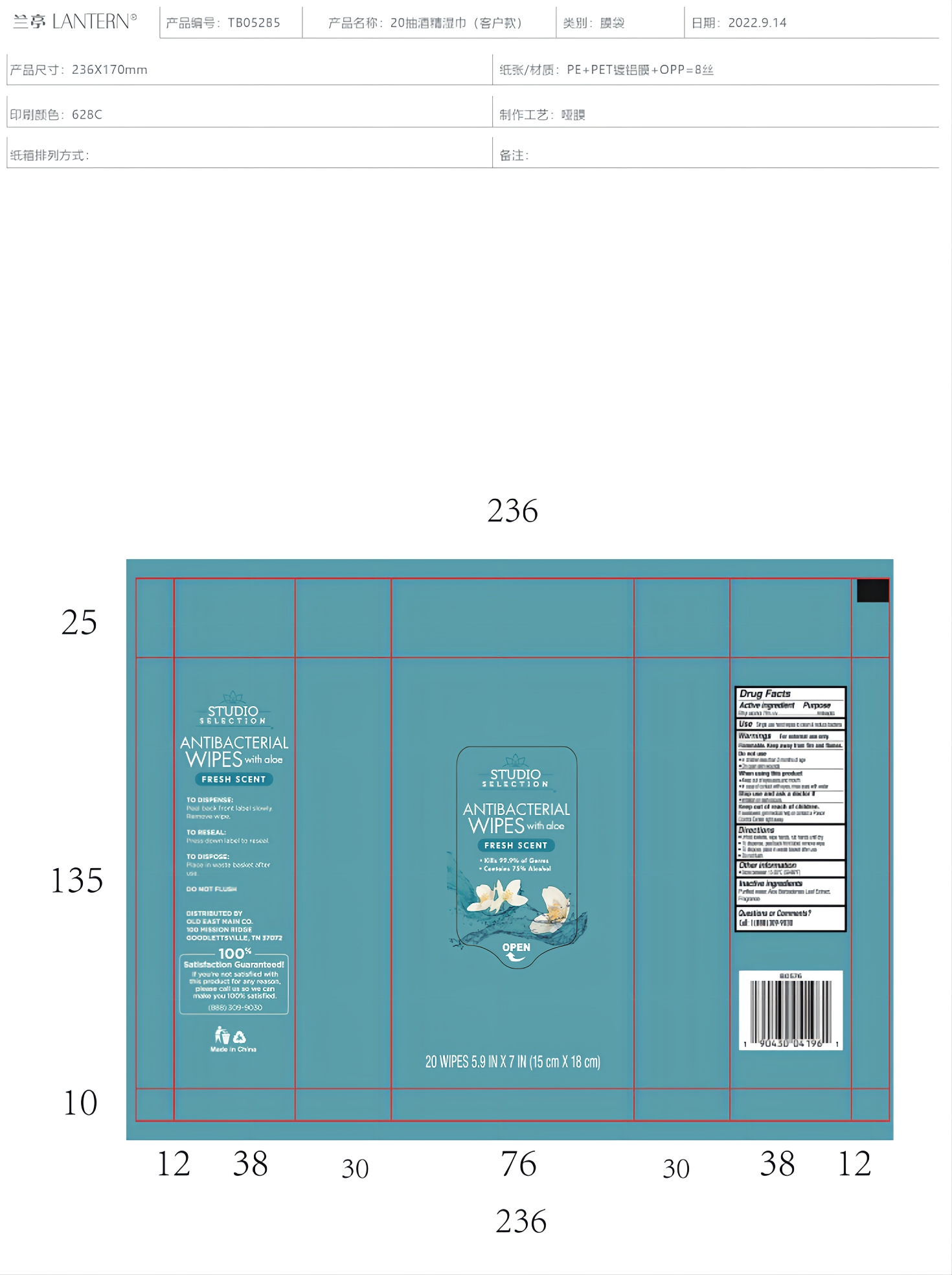 DRUG LABEL: antibacterial wipes with aloe 20wipes
NDC: 54860-400 | Form: CLOTH
Manufacturer: Shenzhen Lantern Science Co.,Ltd.
Category: otc | Type: HUMAN OTC DRUG LABEL
Date: 20221013

ACTIVE INGREDIENTS: ALCOHOL 75 mL/100 mL
INACTIVE INGREDIENTS: WATER 24.7 mL/100 mL; FRAGRANCE 13576 0.1 mL/100 mL; ALOE VERA LEAF 0.2 mL/100 mL

Antibacterial wips with aloe 20wipes

Active ingredient

Active ingredient purpose

Ethyl alcohol 75%V/V Antiseptic

use

Single use hand wipes to clean ＆ reduce bacteria

warnings

For external use only.Flammable. Keep away from fire or flames.

Do not use

in children less than 2 months of age.

on open skin wounds.

When using this product

Keep out of eyes, ears ,and mouth.In case of contact with eyes,rinse eyes with water.

Stop use and ask a doctor

if iritation or rash occurs.

Keep out of reach of children

if swallowed,get medical help or contact a Poison Control Center right away.

Directions

Unfold towlette,wipe hands,rub hands until dry.

To dispense,peel back front lable,remove wipe.

To dispose,place in waste basket after use.

Do not flush.

Other information

Store between15-30℃(59-86F)

Inactive ingredient

Purified water,Aloe Barbadensis Leaf Extract,Fragrance

Usage

TO DISPENSE:
Peel back front label slowly.
Remove wipe.

TO RESEAL:
Press down label to reseal.

TO DISPOSE:
Place in waste basket after use.
DO NOT FLUSH